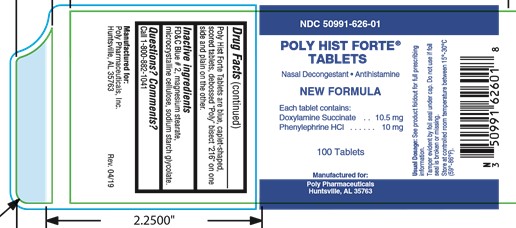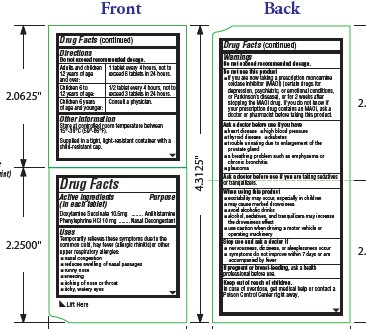 DRUG LABEL: Poly Hist Forte
NDC: 50991-626 | Form: TABLET
Manufacturer: Poly Pharmaceuticals, Inc.
Category: otc | Type: HUMAN OTC DRUG LABEL
Date: 20240709

ACTIVE INGREDIENTS: DOXYLAMINE SUCCINATE 10.5 mg/1 1; PHENYLEPHRINE HYDROCHLORIDE 10 mg/1 1
INACTIVE INGREDIENTS: FD&C BLUE NO. 2; MAGNESIUM STEARATE; CELLULOSE, MICROCRYSTALLINE; SODIUM STARCH GLYCOLATE TYPE A POTATO

Poly Hist Forte

Drug Facts

Active ingredients

(in each tablet)

Doxylamine Succinate 10.5mg

Purpose

Antihistamine

Active ingredients

(in each tablet)

Phenylephrine HCl 10 mg

Purpose

Nasal Decongestant

Uses

Temporarily relieves these symptoms due to the common cold, hay fever (allergic rhinitis)or other upper respiratory allergies:

- nasal congestion
- reduces swelling of nasal passages
- runny nose
- sneezing
- itching of nose or throat
- itchy, watery eyes

Do not use this product

- if you are now taking a prescription monoamine oxidase inhibitor (MAOI) (certain drugs for depression, psychiatric, or emotional conditions, or Parkinson’s disease), or for 2 weeks after stopping the MAOI drug. If you do not know if your prescription drug contains an MAOI, ask a doctor or pharmacist before taking this product.

Ask a doctor before use if you have

- heart disease
- high blood pressure
- thyroid disease
- diabetes
- trouble urinating due to enlargement of the prostate gland
- a breathing problem such as emphysema or chronic bronchitis
- glaucoma

Ask a doctor before use if

you are taking sedatives or tranquilizers.

When using this product

- excitability may occur, especially in children
- may cause marked drowsiness
- avoid alcoholic drinks
- alcohol, sedatives, and tranquilizers may increase the drowsiness effect
- use caution when driving a motor vehicle or operating machinery

Stop use and ask a doctor if

- nervousness, dizziness, or sleeplessness occur
- symptoms do not improve within 7 days or are accompanied by fever

If pregnant or breast-feeding,

ask a health professional before use.

Keep out of reach of children.

In case of overdose, get medical help or contact a Poison Control Center right away.

Directions

Do not exceed recommended dosage.

Adults and children 12 years of age and over | 1 tablet every 4 hours, not to exceed 6 tablets in 24 hours.
Children 6 to 12 years of age: | 1/2 tablet every 4 hours, not to exceed 3 tablets in 24 hours.
Children 6 years of age and younger: | Consult a physician.

Other information

Store at controlled room temperature between 15°-30°C (59°-86°F).

Supplied in a tight, light-resistant container with a child-resistant cap.

Poly Hist Forte Tablets are blue, caplet-shaped, scored tablets, debossed "Poly" bisect "216" on one side and plain on the other.

Inactive ingredients

FD&C Blue # 2, magnesium stearate, microcrystalline cellulose, sodium starch glycolate.

Questions? Comments?

Call 1-800-882-1041

Manufactured for:

Poly Pharmaceuticals, Inc.

Huntsville, AL Rev. 4/16

PRINCIPAL DISPLAY PANEL

NDC 50991-626-01
POLY HIST FORTE ®
TABLETS
Nasal Decongestant • Antihistamine
NEW FORMULA
Each tablet contains:
Doxylamine Succinate . . . 10.5 mg
Phenylephrine HCl . . . . . . 10 mg
100 Tablets